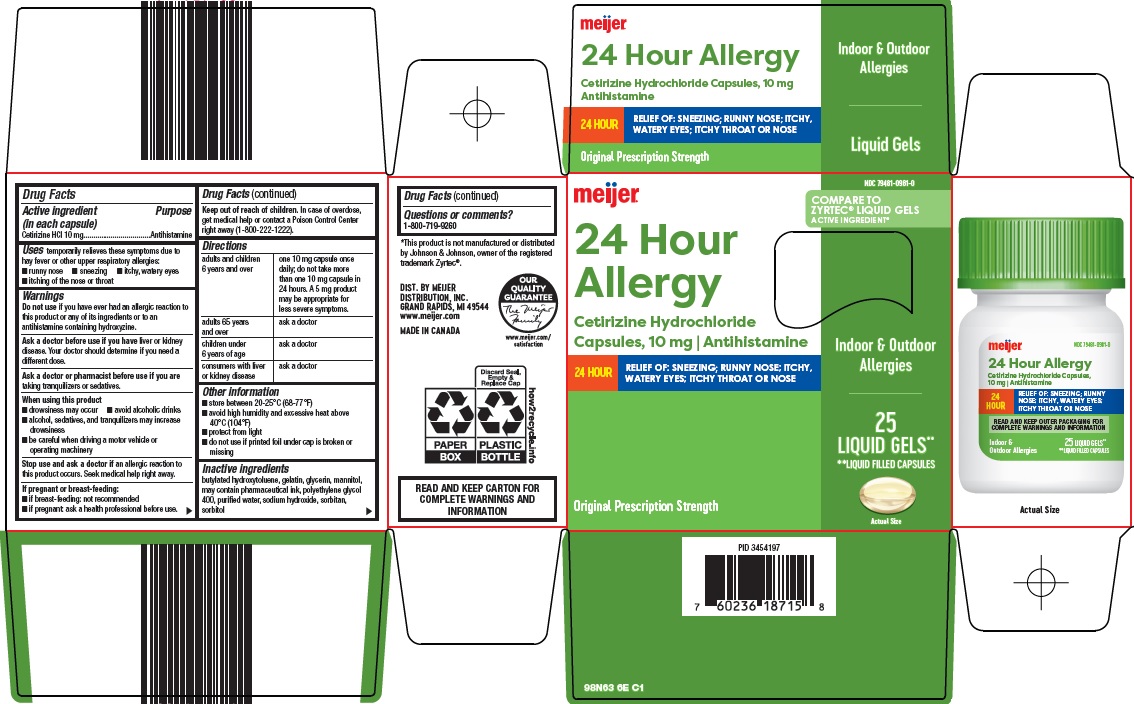 DRUG LABEL: 24 hour allergy
NDC: 79481-0981 | Form: CAPSULE, LIQUID FILLED
Manufacturer: Meijer, Inc.
Category: otc | Type: HUMAN OTC DRUG LABEL
Date: 20250418

ACTIVE INGREDIENTS: CETIRIZINE HYDROCHLORIDE 10 mg/1 1
INACTIVE INGREDIENTS: BUTYLATED HYDROXYTOLUENE; GELATIN, UNSPECIFIED; GLYCERIN; MANNITOL; POLYETHYLENE GLYCOL 400; WATER; SODIUM HYDROXIDE; SORBITAN; SORBITOL

Meijer Distribution, Inc. 24 Hour Allergy Drug Facts

Active ingredient (in each capsule)

Cetirizine HCl 10 mg

Purpose

Antihistamine

Uses

temporarily relieves these symptoms due to hay fever or other upper respiratory allergies:

- runny nose
- sneezing
- itchy, watery eyes
- itching of the nose or throat

Warnings

Do not use

if you have ever had an allergic reaction to this product or any of its ingredients or to an antihistamine containing hydroxyzine.

Ask a doctor before use if you have

liver or kidney disease. Your doctor should determine if you need a different dose.

Ask a doctor or pharmacist before use if you are

taking tranquilizers or sedatives.

When using this product

- drowsiness may occur
- avoid alcoholic drinks
- alcohol, sedatives, and tranquilizers may increase drowsiness
- be careful when driving a motor vehicle or operating machinery

Stop use and ask a doctor if

an allergic reaction to this product occurs. Seek medical help right away.

If pregnant or breast-feeding:

- if breast-feeding: not recommended
- if pregnant: ask a health professional before use.

Keep out of reach of children.

In case of overdose, get medical help or contact a Poison Control Center right away (1-800-222-1222).

Directions

adults and children 6 years and over | one 10 mg capsule once daily; do not take more than one 10 mg capsule in 24 hours. A 5 mg product may be appropriate for less severe symptoms.
adults 65 years and over | ask a doctor
children under 6 years of age | ask a doctor
consumers with liver or kidney disease | ask a doctor

Other information

- store between 20-25°C (68-77°F)
- avoid high humidity and excessive heat above 40°C (104°F)
- protect from light
- do not use if printed foil under cap is broken or missing

Inactive ingredients

butylated hydroxytoluene, gelatin, glycerin, mannitol, may contain pharmaceutical ink, polyethylene glycol 400, purified water, sodium hydroxide, sorbitan, sorbitol

Questions or comments?

1-800-719-9260

Package/Label Principal Display Panel

meijer®

COMPARE TO ZYRTEC® LIQUID GELS ACTIVE INGREDIENT

24 Hour Allergy

Cetirizine Hydrochloride Capsules, 10 mg | Antihistamine

Indoor & Outdoor Allergies

24 HOUR

RELIEF OF: SNEEZING; RUNNY NOSE; ITCHY, WATERY EYES; ITCHY THROAT OR NOSE

25 LIQUID GELS**

**LIQUID FILLED CAPSULES

Actual Size

Original Prescription Strength